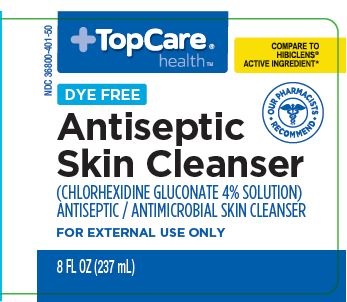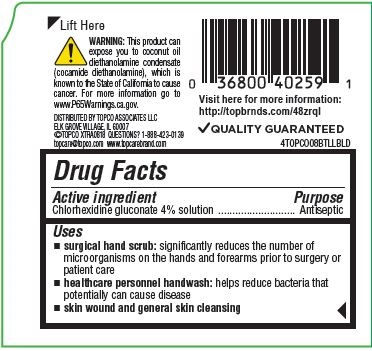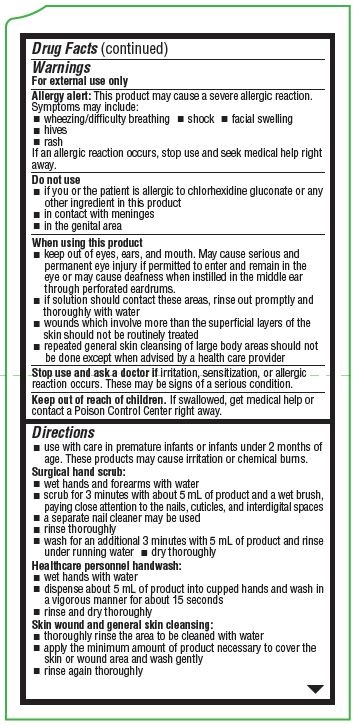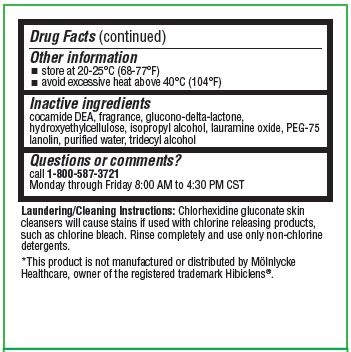 DRUG LABEL: Antiseptic Skin Cleanser
NDC: 36800-401 | Form: LIQUID
Manufacturer: Topco Associates LLC
Category: otc | Type: HUMAN OTC DRUG LABEL
Date: 20251212

ACTIVE INGREDIENTS: CHLORHEXIDINE GLUCONATE 4 mg/100 mL
INACTIVE INGREDIENTS: COCO DIETHANOLAMIDE; PEG-75 LANOLIN; HYDROXYETHYL CELLULOSE (2000 CPS AT 1%); ISOPROPYL ALCOHOL; WATER; TRIDECYL ALCOHOL; GLUCONOLACTONE

COMP TopCo/TopCare 4% 8oz

Active Ingredient

Chlorhexidine Gluconate 4% Solution

Purpose

Antiseptic

Uses

- surgical hand scrub: significantly reduces the number of microorganisms on the hands and forearms prior to surgery or patient care
- healthcare personnel handwash: helps reduce bacteria that potentially can cause disease
- skin wound and general skin cleansing

Warnings

For external use only

Allergy alert: This product may cause a severe allergic reaction. Symptoms may include:

- wheezing/difficulty breathing
- shock
- facial swelling
- hives
- rash

If an allergic reaction occurs, stop use and seek medical help right away

Do not use

- if you or the patient is allergic to chlorhexidine gluconate or any other ingredient in this product
- in contact with meninges
- in the genital area

Keep out of reach of children.

If swallowed, get medical help or contact a Poison Control Center right away.

Stop use and ask a doctor if

irritation, sensitization or allergic reaction occurs. These may be signs of a serious condition.

When using this product

- keep out of eyes, ears, and mouth. May cause serious and permanent eye injury if permitted to enter and remain in the eye or may cause deafness when instilled in the middle ear through perforated eardrums.
- if solution should contact these areas, rinse out promptly and thoroughly with water
- wounds which involve more than the superficial layers of the skin should not be routinely treated
- repeated general skin cleansing of large body areas should not be done except when advised by a health care provider

Directions

use with care in premature infants or infants under 2 months of age. These products may cause irritation or chemical burns.

Surgical hand scrub

- wet hands and forearms under running water
- scrub for 3 minutes with about 5 mL of product and a wet brush, paying close attention to the nails, cuticles, and interdigital spaces
- a separate nail cleaner may be used
- rinse thoroughly
- wash for an additional 3 minutes with 5 mL of product and rinse under running water
- dry thoroughly

Healthcare personnel handwash:

- wet hands with water
- dispense about 5 mL of product into cupped hands and wash in a vigorous manner for about 15 seconds
- rinse and dry thoroughly

Skin wound and general skin cleansing:

- thoroughly rinse the area to be cleaned with water
- apply the minimum amount of product necessary to cover the skin or wound area and wash gently
- rinse again thoroughly

Other information

- store at 20-25°C (68-77° F)
- avoid excessive heat above 40°C (104°F)

Inactive ingredients

cocamide DEA, fragrance, glucono-delta-lactone, hydroxyethylcellulose, isopropyl alcohol, lauramine oxide, PEG-75 lanolin, purified water, tridecyl alcohol.

Questions of comments?

call 1-800-587-3721 Monday through Friday 8:00 AM to 4:30 PM CST

OTHER SAFETY INFORMATION

Warning: This product can expose you to coconut oil diethanolamine condensate (cocamide diethanolamine), which is known to the State of California to cause cancer. For more information go to www.P65Warnings.gov

Laundering/Cleaning Instructions: Chlorhexidine gluconate skin cleansers will cause stains if used with chlorine releasing products. Rinse completely and use only non-chlorine detergents.

*This product is not manufactured or distributed by Mölnlycke Healthcare, owner of the registered trademark Hibiclens®.

Package label and principal display panel

NDC 36800-401-50

TopCare® health™

COMPARE TO HIBICLENS® ACTIVE INGREDIENT*

DYE FREE

Antiseptic Skin Cleanser

(CHLORHEXIDINE GLUCONATE 4% SOLUTION)

ANTISEPTIC / ANTIMICROBIAL SKIN CLEANSER

FOR EXTERNAL USE ONLY

8 FL OZ (237 mL)